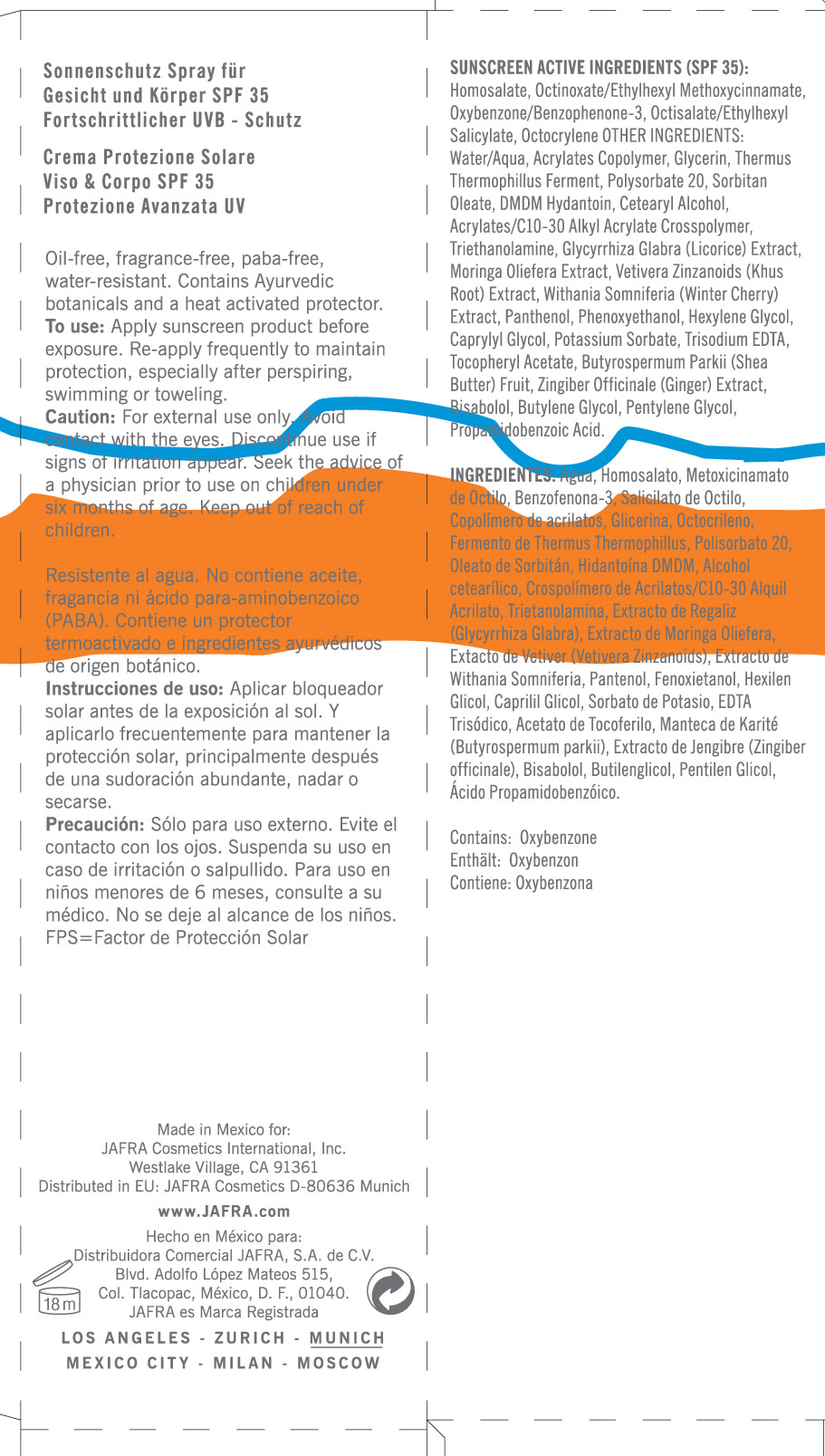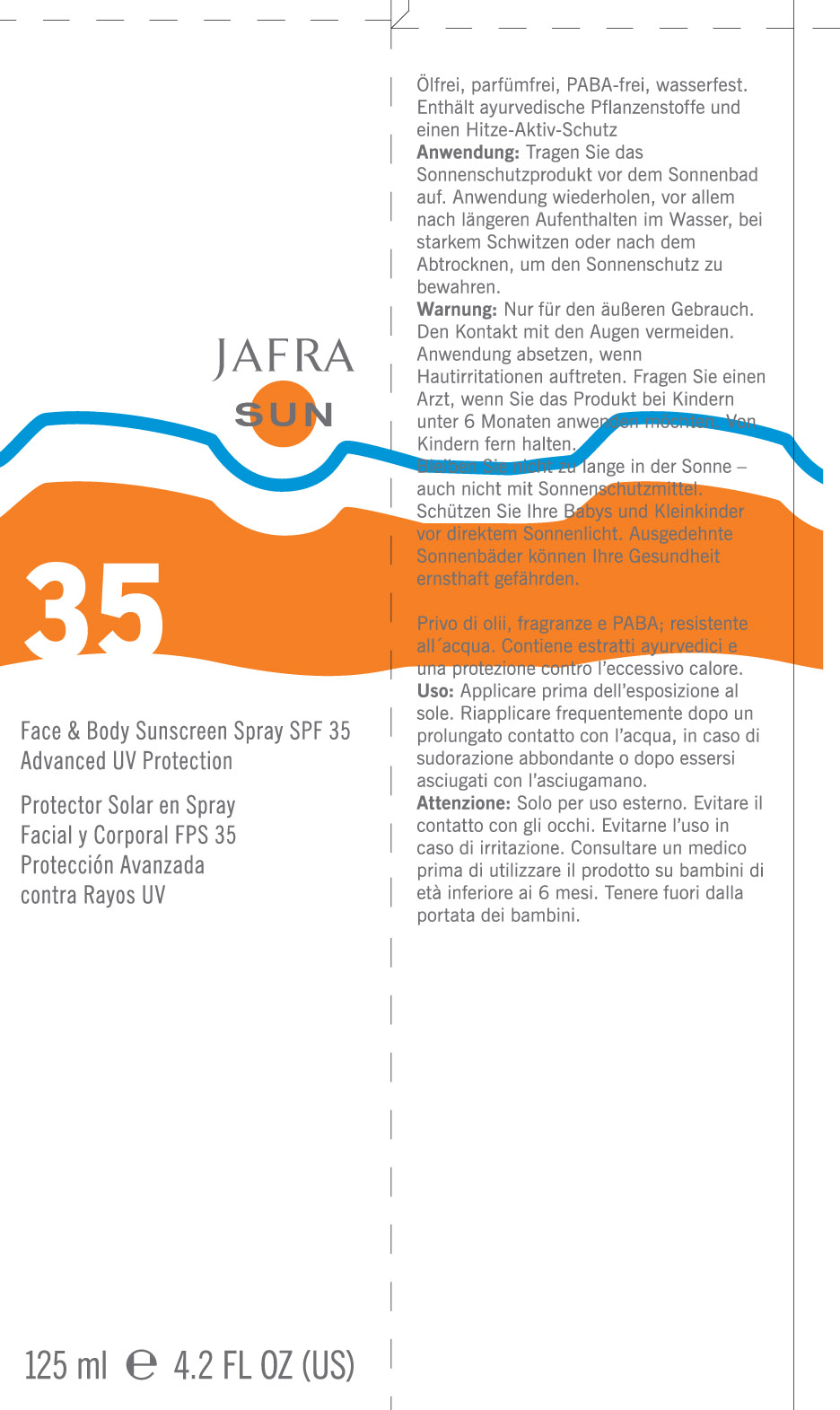 DRUG LABEL: Face and Body Sunscreen Spray
NDC: 68828-092 | Form: LOTION
Manufacturer: Jafra Cosmetics International Inc
Category: otc | Type: HUMAN OTC DRUG LABEL
Date: 20120605

ACTIVE INGREDIENTS: HOMOSALATE 10 mL/100 mL; OCTINOXATE 3 mL/100 mL; OXYBENZONE 6 mL/100 mL; OCTISALATE 5 mL/100 mL; OCTOCRYLENE 2.79 mL/100 mL
INACTIVE INGREDIENTS: WATER; GLYCERIN; POLYSORBATE 20; SORBITAN MONOOLEATE; DMDM HYDANTOIN; CETOSTEARYL ALCOHOL; CARBOMER INTERPOLYMER TYPE A (55000 MPA.S) ; TROLAMINE; GLYCYRRHIZA GLABRA; MORINGA OLEIFERA BARK; WITHANIA SOMNIFERA ROOT; PANTHENOL; PHENOXYETHANOL; HEXYLENE GLYCOL; CAPRYLYL GLYCOL; POTASSIUM SORBATE; EDETATE TRISODIUM; .ALPHA.-TOCOPHEROL ACETATE; SHEANUT OIL; GINGER; LEVOMENOL; BUTYLENE GLYCOL; PENTYLENE GLYCOL

Face and Body Sunscreen Spray SPF 35

Sunscreen active ingredients (SPF 35):

Homosalate, Octinoxate/Ethylhexyl Methoxycinnamate , Oxybenzone/Benzophenone-3, Octisalate/Ethylhexyl Salicylate, Octocrylene

Purpose: Sunscreen

Keep out of reach of children

INDICATIONS AND USAGE

Discontinue use if signs of irritation appear.

WARNINGS

Caution: For external use only. Avoid contact with eyes. Seek the advice of a physician prior to use on children under six months of age.

DOSAGE AND ADMINISTRATION

To use: Apply sunscreen product before exposure. Re-apply frequently to maintain protection, especially after perspiring, swimming, or toweling.

INACTIVE INGREDIENT

Other Ingredients:
Water/Aqua, Acrylates Copolymer, Glycerin, Thermus Thermophillus Ferment, Polysorbate 20, Sorbitan Oleate, DMDM Hydantoin, Cetearyl Alcohol, Acrylates/C10-30 Alkyl Acrylate Crosspolymer, Trethanolamine, Glycyrrhiza Glabra (Licorice) Extract, Moringa Oliefera Extract, Vetivera Zinzanoids (Khus Root) Extract, Withania Somnifera (winter Cherry) Extract, Panthenol, Phenoxyethanol, Hexylene Glycol, Caprylyl Glycol, Potassium Sorbate, Trisodium EDTA, Tocopheryl Acetate, Butyrospermum Parkii (Shea Butter) Fruit, Zingiber Officinale (Ginger) Extract, Bisabolol, Butylene Glycol, Pentylene Glycol, Propamidobenzoic Acid.

PACKAGE LABEL

Jafra Sun

Face and Body Sunscreen Spray SPF 35

Advanced UV protection

Protector Solar en Spray

Facial y Corporal FPS 35

Proteccion Avanzada

contra rayos